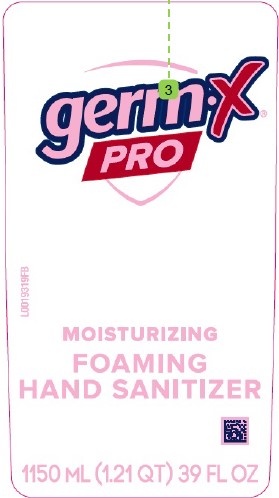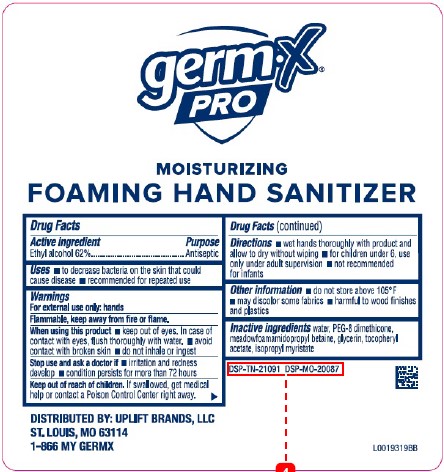 DRUG LABEL: Moisturizing Hand Sanitizer
NDC: 83986-447 | Form: GEL
Manufacturer: UpLift Brands, LLC
Category: otc | Type: HUMAN OTC DRUG LABEL
Date: 20250513

ACTIVE INGREDIENTS: ALCOHOL 62 mL/100 mL
INACTIVE INGREDIENTS: WATER; PEG-8 DIMETHICONE; MEADOWFOAMAMIDOPROPYL BETAINE; GLYCERIN; .ALPHA.-TOCOPHEROL ACETATE; ISOPROPYL MYRISTATE

Germ-X 447.001/447AC
Moisturizing Foaming Hand Sanitizer

Claims

germ-x

PRO

MOISTURIZING

FOAMING HAND SANITIZER

Active ingredient

Ethyl alcohol 62%

Purpose

Antiseptic

Uses

- to decrease bacteria on the skin that could cause disease
- recommended for repeated use

Warnings

For external use only: hands

Flammable, keep away from fire or flame.

When using this product

- Keep out of eyes. In case of contact with eyes, flush thoroughly with water.
- avoid contact with broken skin
- do not inhale or ingest

Stop use and ask a doctor if

- irritation and redness develop
- condition persists for more than 72 hours

Keep out of reach of children

If swallowed, get medical help or contact a Poison Control Center right away.

Directions

- wet hands thoroughly with product and allow to dry without wiping
- for children under 6, use only under adult supervision
- not recommended for infants

Other information

- do not store above 105°F
- may discolor some fabrics
- harmful to wood finishes and plastics

Inactive ingredients

water, PEG-8 dimethicone, meadowfoamamidopropyl betaine, glycerin, tocopheryl acetate, isopropyl myristate

Adverse Reactions

DISTRIBUTED BY: UPLIFT BRANDS, LLC

ST. LOUIS, MO 63114

1-866 MY GERMX

DSP-TN-21091 DSP-MO-20087

Principal display panel

germ-X®

PRO

MOISTURIZING

FOAMING

HAND SANITIZER

1150 mL (1.21 QT) 39 FL OZ